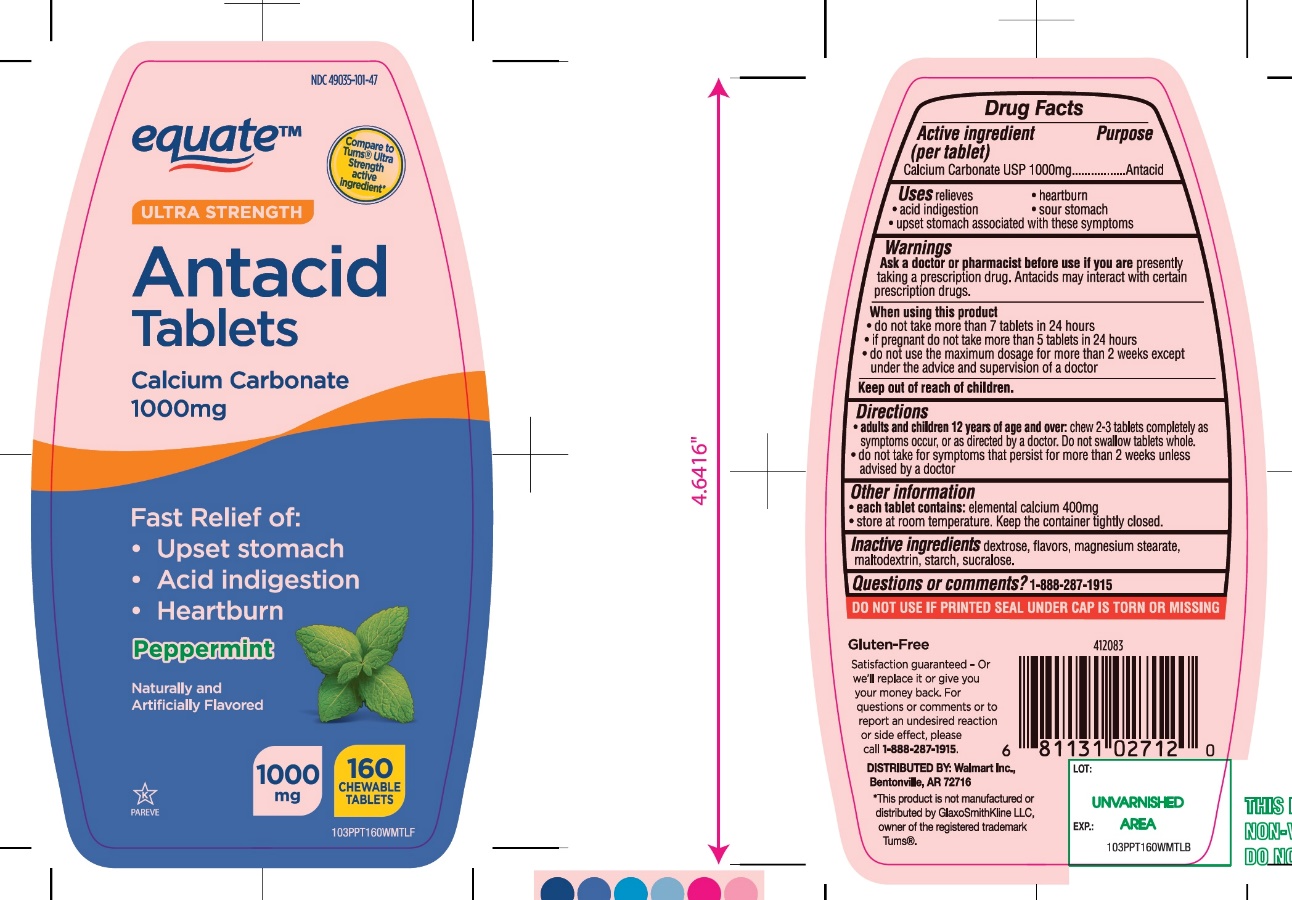 DRUG LABEL: equate Ultra Strength Antacid

NDC: 49035-101 | Form: TABLET, CHEWABLE
Manufacturer: Wal-Mart Stores,Inc.,
Category: otc | Type: HUMAN OTC DRUG LABEL
Date: 20251027

ACTIVE INGREDIENTS: CALCIUM CARBONATE 1000 mg/1 1
INACTIVE INGREDIENTS: DEXTROSE, UNSPECIFIED FORM; MAGNESIUM STEARATE; MALTODEXTRIN; STARCH, CORN; SUCRALOSE

equate Ultra Strength Antacid Calcium Carbonate Chewable Tablets

Active ingredient (per tablet)

Calcium Carbonate USP 1000mg

Purpose

Antacid

Uses

relieves

- heartburn
- acid indigestion
- sour stomach
- upset stomach associated with these symptoms

Warnings

Ask a doctor or pharmacist before use if you arepresently taking a prescription drug. Antacids may interact with certain prescription drugs.

When using this product

- do not take more than 7 tablets in 24 hours
- if pregnant do not take more than 5 tablets in 24 hours
- do not use the maximum dosage for more than 2 weeks except under the advice and supervision of a doctor.

Directions

- adults and children 12 years of age and over:chew 2-3 tablets as symptoms occur, or as directed by a doctor
- do not take for symptoms that persist for more than 2 weeks unless advised by a doctor

Other information

- each tablet contains:elemental calcium 400mg
- Store at room temperature. Keep the container tightly closed.

Inactive ingredients

dextrose, flavors, magnesium stearate, maltodextrin, starch, sucralose.

Questions?

1-888-287-1915

Safety sealed: Do not use if printed seal under cap is torn or missing

Package/Label Principal Display Panel

NDC 49035-101-47

equate™

Compare to Tums® Ultra Strength Active Ingredient*

Ultra Strength

Antacid

Calcium Carbonate

Starts Working in Seconds to Relieve:

- Heartburn
- Acid indigestion
- Sour stomach

Peppermint Flavor

1000 mg

160 CHEWABLE TABLETS

Gluten- Free

Satisfaction guaranteed-Or we’ll replace it or give you your money back. For questions or comments or to report an undesired reaction or side effect, please call 1-888-287-1915.

DISTRIBUTED BY: Wal-Mart Stores, Inc.,

Bentonville, AR 72716

*This product is not manufactured or distributed by GlaxoSmithKline LLC, owner of the registered trademark Tums®.